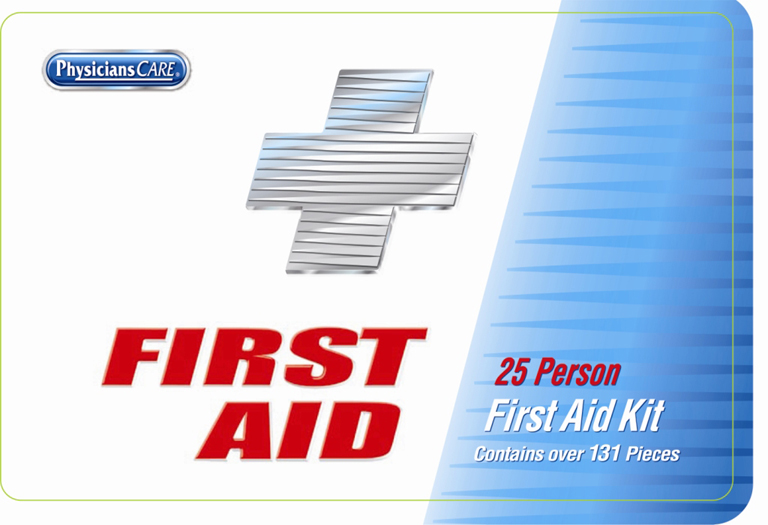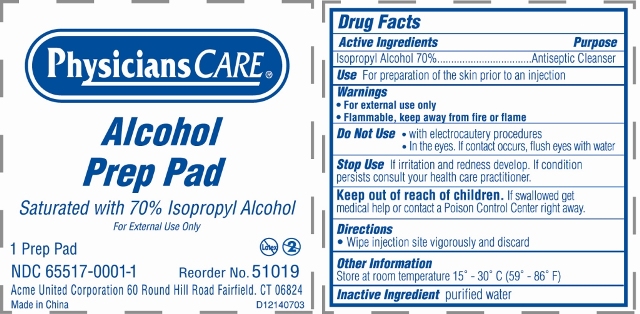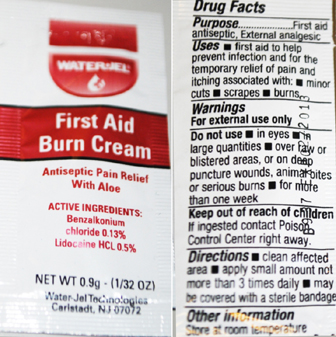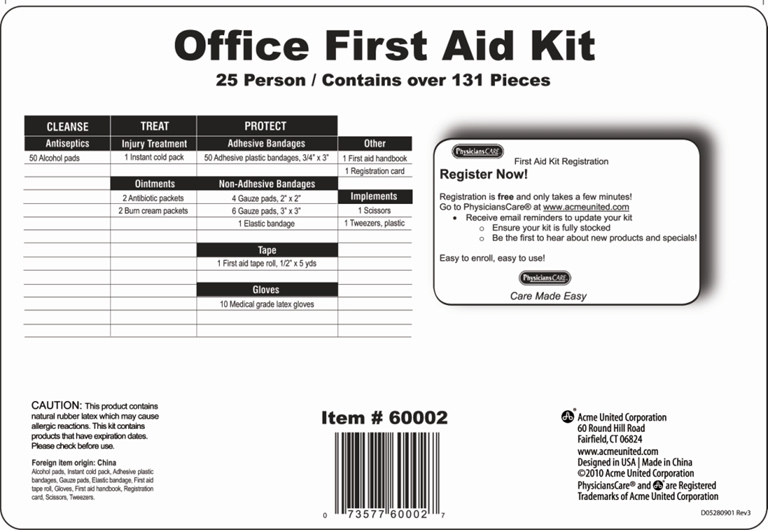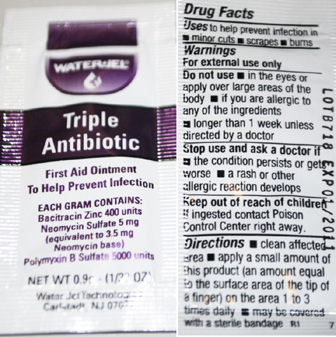 DRUG LABEL: Office First Aid Kit
NDC: 65517-0018 | Form: KIT | Route: TOPICAL
Manufacturer: Dukal Corporation
Category: other | Type: MEDICAL DEVICE
Date: 20100920

ACTIVE INGREDIENTS: ISOPROPYL ALCOHOL 0.70 mL/1.0 mL; BACITRACIN ZINC 400 [iU]/1 g; NEOMYCIN SULFATE 3.5 mg/1 g; POLYMYXIN B SULFATE 5000 [iU]/1 g; BENZALKONIUM CHLORIDE 0.13 g/100 g; LIDOCAINE HYDROCHLORIDE 0.5 g/100 g
INACTIVE INGREDIENTS: PETROLATUM; EDETATE DISODIUM; LIGHT MINERAL OIL; STEARIC ACID; POLYETHYLENE GLYCOL; CETYL ALCOHOL; TROLAMINE; GLYCERIN; METHYLPARABEN; PROPYLENE GLYCOL; DIAZOLIDINYL UREA; ALOE VERA LEAF; WATER; PROPYLPARABEN; GLYCERYL MONOSTEARATE

Content Card

HOW SUPPLIED

Office First Aid Kit

25 Person / Contains over 131 pieces

CLEANSE

Antiseptics

50 Alcohol Pads

TREAT

Injury Treatment

1 Instant cold pack

Ointments

2 Antibiotic packets
2 Burn cream packets

PROTECT

Adhesive Bandages

50 Adhesive plastic bandages, 3/4” x 3”

Non-Adhesive Bandages

4 Gauze pads 2" x 2"
6 Gauze pads 3" x 3'
1 Elastic bandage

Tape
1 First aid tape roll, 1/2” x 5 yds
Gloves
10 Medical grade gloves
Other
1 First aid handbook
1 Registration card
Implements
1 Scissors
1 Tweezers, plastic

GENERAL PRECAUTIONS

CAUTION: This product contains
natural rubber latex which may cause
allergic reactions. This kit contains
products that have expiration dates.
Please check before use.

REFERENCES

Foreign item origin: China
Alcohol Pads, Instant cold pack, Adhesive
plastic bandages, Gauze pads, Elastic bandage,
First aid tape roll, Gloves, First aid handbook,
Registration card, Scissors,Tweezers.

PACKAGE LABEL

Acme United Corporation
60 Round Hill Road
Fairfield, CT 06824

www.acmeunited.com
Designed in the USA | Made in China
©2010 Acme United Corporation

PhysiciansCare® and Acme are registered
trademarks of Acme United Corporation.

Prep Pad Labeling

Reorder 51019

NDC 65517-0001-1

Physicians Care

Alcohol Prep Pad

Saturated with 70% Isopropyl Alcohol

For External Use Only

1 Prep Pad

Acme United Corporation, 60 Round Hill Road, Fairfield, CT 06824

Made in China

Drug Facts

Active Ingredients..................... Isopropyl Alcohol 70%

Purpose................................. Antiseptic Cleanser

Use For preparation of the skin prior to an injection

Warnings

- For External Use Only
- Flammable. Keep away from fire or flame

Do Not Use

- with electrocautery procedures.
- In the eyes. If contact occurs, flush eyes with water.

Stop Use

If irritation or redness develop.

If condition persists, consult your health care practitioner.

Keep out of reach of children. If swallowed get medical help or

contact a Poison Control Center right away.

Directions

Wipe injection site vigorously and discard.

Other Information

Store at Room Temperature 15 - 30 C (59 - 86 F)

Inactive Ingredient purified water

Triple Antibiotic Labeling

WaterJel

Triple Antibiotic

First Aid Ointment

To Help Prevent Infection

Each Gram contains

Bacitracin Zinc 400 units

Neomycin Sulphate 5 mg

(equivalent to 3.5 mg Neomycin base)

Polymyxin B Sulfate 5000 units

Water-Jel Technologies

Carlstadt, NJ 07072

Drug Facts

Uses to help prevent infection in

minor cuts, scrapes, burns

Warnings

For external use only

Do not use

in the eyes or apply over large areas of the body

If you are allergic to any of the ingredients

longer than 1 week unless directed by a doctor

Stop use and ask a doctor if

the condition persists or gets worse

a rash or other allergic reaction develops

Keep out of reach of children

if ingested contact Poison Control Center right away

Directions

clean affected area apply a small amount of product

(an amount equal to the surface area of the tip of a finger)

on the area 1 to 3 times daily may be covered with a sterile bandage

First Aid Burn Cream Labeling

WaterJel

First Aid Burn Cream

Antiseptic Pain Relief with Aloe

Active Ingredients:

Benzalkonium Chloride 0.13%

Lidocaine HCL 0.5%

Water-Jel Technologies

Carlstadt, NJ 07072

Drug Facts

Purpose

First Aid Antiseptic, External analgesic

Uses

first aid to help prevent infection and for temporary

relief of pain an itching associated with minor cuts,

scrapes, burns

Warnings

For external use only

Do not use

in the eyes

in large quantities over raw or blistered areas or on

deep puncture wounds, animal bites, or serious burns

Keep out of reach of children

if ingested contact Poison Control Center right away

Directions

clean affected area apply a small amount not more

than 3 times daily may be covered with a sterile bandage

Other Information

Store at room temperature